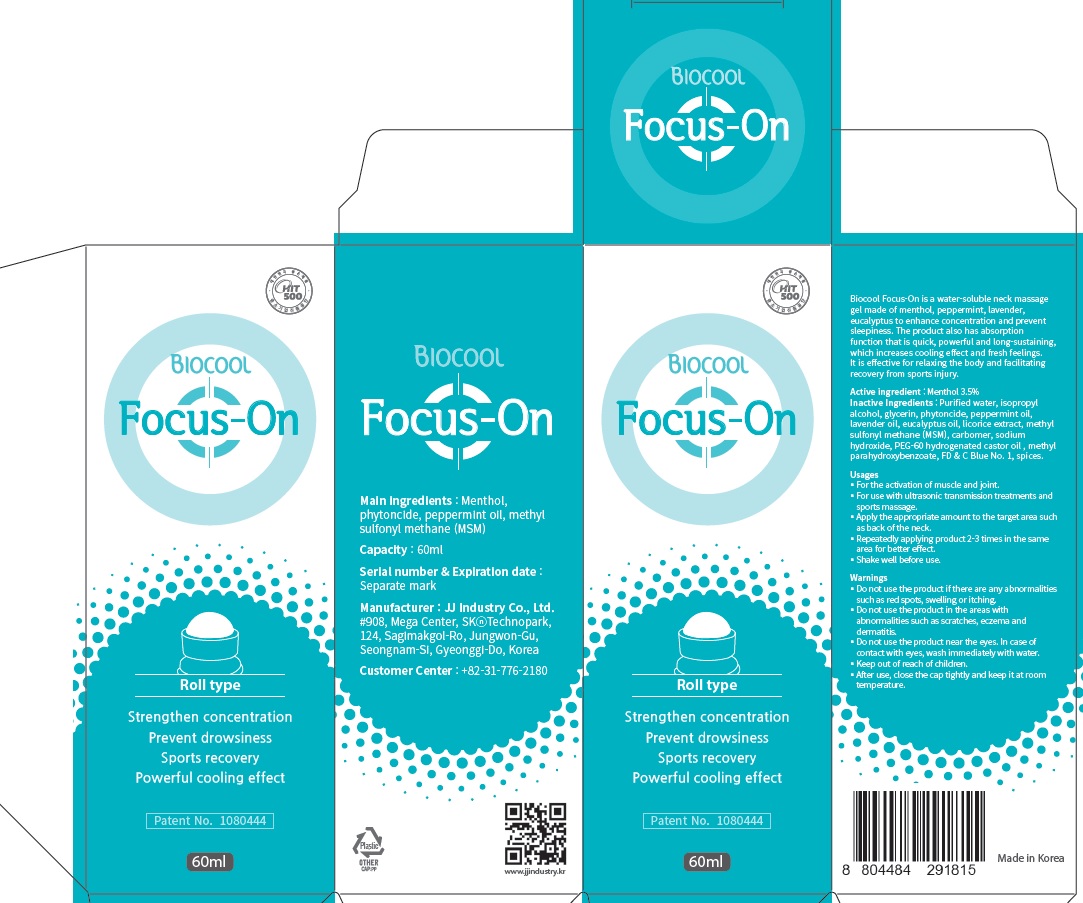 DRUG LABEL: Biocool Focus On
NDC: 70612-030 | Form: GEL
Manufacturer: JJindustry.Co.Ltd
Category: otc | Type: HUMAN OTC DRUG LABEL
Date: 20181101

ACTIVE INGREDIENTS: Menthol 2.1 g/60 mL
INACTIVE INGREDIENTS: Water; Glycerin

ACTIVE INGREDIENT

Active ingredients: Menthol 3.5%

INACTIVE INGREDIENT

Inactive ingredients:

Purified water, isopropyl alcohol, glycerin, phytoncide, peppermint oil, lavender oil, eucalyptus oil, licorice extract, methyl sulfonyl methane,
carbomer, sodium hydroxide, PEG-60 hydrogenated castor oil , methyl parahydroxybenzoate, FD & C

PURPOSE

Purpose: Topical Analgesic

WARNINGS

▪ Do not use the product if there are any abnormalities such as red spots, swelling or itching.

▪ Do not use the product in the areas with abnormalities such as scratches, eczema and dermatitis.

▪ Do not use the product near the eyes. In case of contact with eyes, wash immediately with water.

▪ Keep out of reach of children.

▪ After use, close the cap tightly and keep it at room temperature.

KEEP OUT OF REACH OF CHILDREN

Usages

Usages: For the activation of muscle and joint. For use with ultrasonic transmission treatments and sports massage. Apply appropriate amount onto affected area and rub until fully absorbed. It's more effective when applied 2~3 times repeatedly.

Usages

Usages: For the activation of muscle and joint. For use with ultrasonic transmission treatments and sports massage. Apply appropriate amount onto affected area and rub until fully absorbed. It's more effective when applied 2~3 times repeatedly.